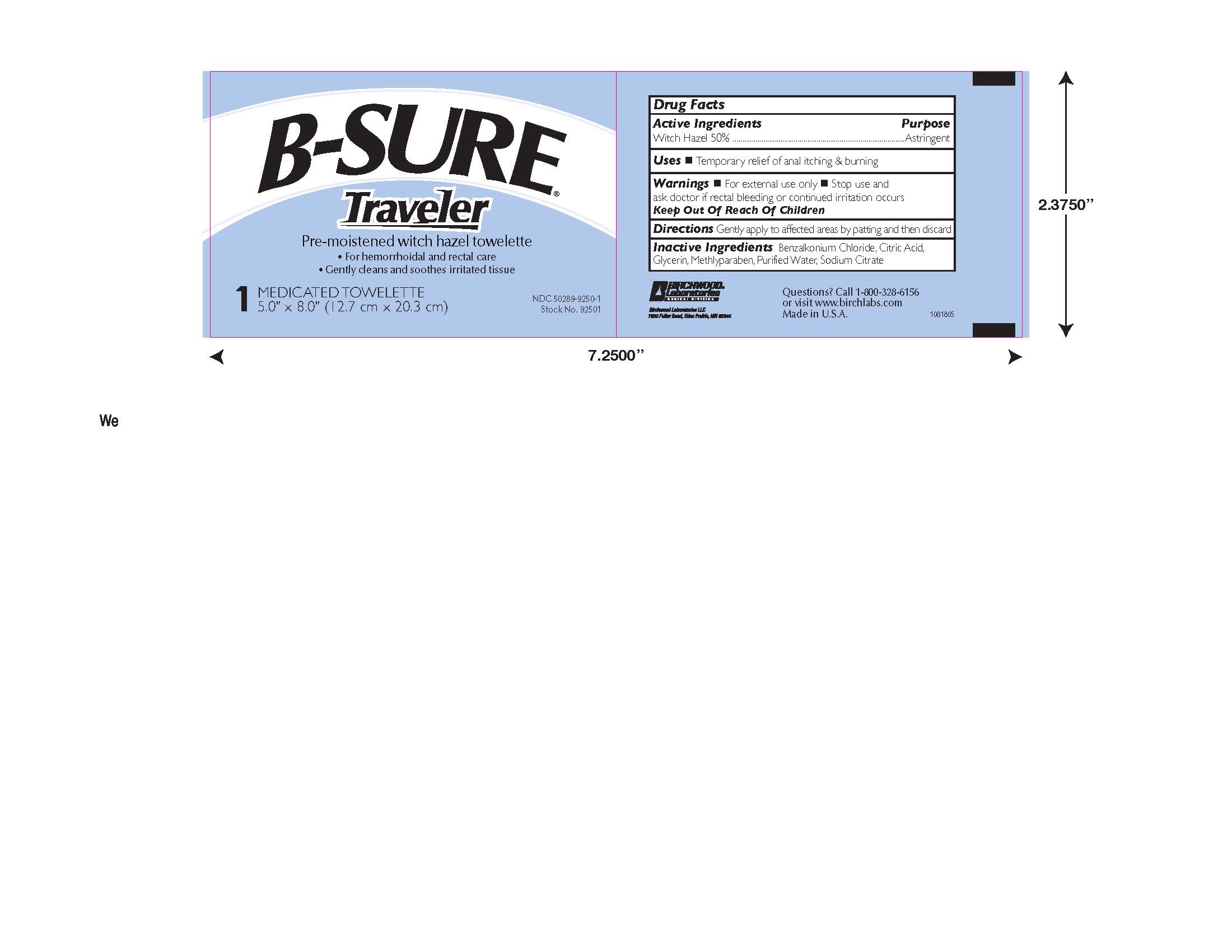 DRUG LABEL: B-SURE Traveler Towelette
NDC: 50289-9250 | Form: SOLUTION
Manufacturer: Birchwood Laboratories LLC
Category: otc | Type: HUMAN OTC DRUG LABEL
Date: 20250114

ACTIVE INGREDIENTS: WITCH HAZEL 0.5 g/1 g
INACTIVE INGREDIENTS: GLYCERIN 0.125 g/1 g; SODIUM CITRATE 0.034 g/1 g; ANHYDROUS CITRIC ACID 0.026 g/1 g; METHYLPARABEN 0.012 g/1 g; BENZALKONIUM CHLORIDE 0.0009 g/1 g; WATER 0.302 g/1 g

B-SURE Traveler Drug Facts

Warnings

For external use only. Stop use and ask doctor if rectal bleeding or continued irratation occurs.

Directions

Gently apply to affected areas by patting and then discard.

Inactive Ingredients

Benzalkonium Chloride, Citric Acid, Glycerin, Methlyparaben, Purified Water, Sodium Citrate

Purpose

Astringent

Keep Out of Reach of Children

Uses

Temporary relief of anal itching & burning.

Active Ingredients

Witch Hazel 50%